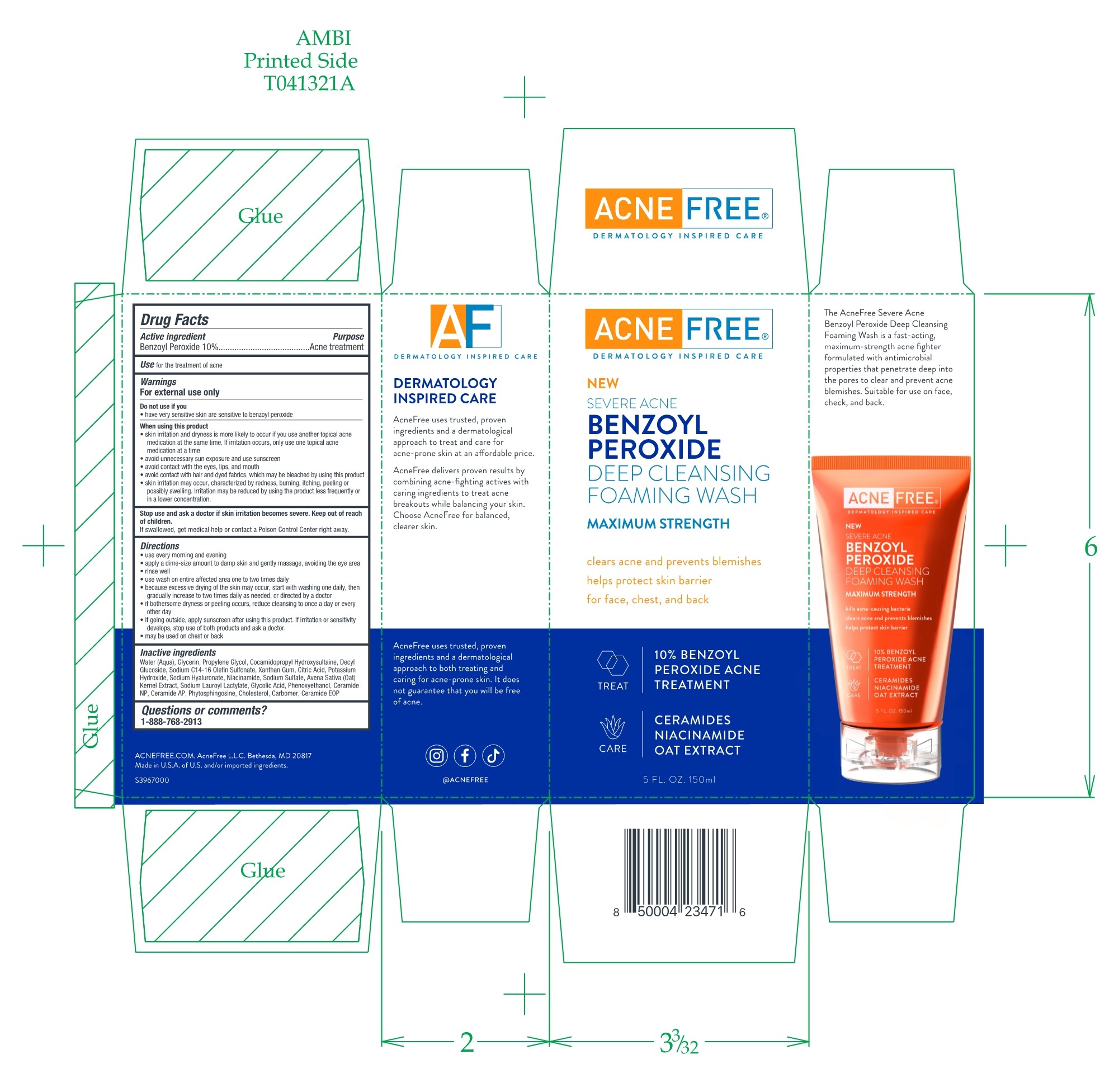 DRUG LABEL: Benzoyl Peroxide Deep Cleansing Foaming Wash
NDC: 80861-112 | Form: CREAM
Manufacturer: AcneFree, LLC
Category: otc | Type: HUMAN OTC DRUG LABEL
Date: 20250724

ACTIVE INGREDIENTS: BENZOYL PEROXIDE 0.1 g/1 g
INACTIVE INGREDIENTS: GLYCERIN; PROPYLENE GLYCOL

Benzoyl Peroxide Deep Cleansing Foaming Wash

ACTIVE INGREDIENT

10 percent Benzoyl Peroxide

Purpose

Acne Treatment

USE

for the treatment of acne

Warnings

For external use only

Do not use if you

have very sensitive skin are sensitive to benzoyl peroxide

When using this product

• skin irritation and dryness is more likely to occur if you use another topical acne medication at the same time. If irritation occurs, only use one topical acne medication at a time

• avoid unnecessary sun exposure and use sunscreen

• avoid contact with the eyes, lips, and mouth

• avoid contact with hair and dyed fabrics, which may be bleached by using this product

• skin irritation may occur, characterized by redness, burning, itching, peeling or possibly swelling. Irritation may be reduced by using the product less frequently or in a lower concentration.

Stop use and sk a doctor if skin irritation becomes severe. Keep out of reach of children.

If swallowed, get medical help or contact a Poison Control Center right away

Keep out of reach of children

Directions

use every morning and evening

• apply a dime-size amount to damp skin and gently massage, avoiding the eye area

• rinse well

• use wash on entire affected area one to two times daily

• because excessive drying of the skin may occur, start with washing one daily, then gradually increase to two times daily as needed, or directed by a doctor

• if bothersome dryness or peeling occurs, reduce cleansing to once a day or every other day

• if going outside, apply sunscreen after using this product. If irritation or sensitivity develops, stop use of both products and ask a doctor.

• may be used on chest or back

Inactive Ingredients

Water (Aqua), Glycerin, Propylene Glycol, Cocamidopropyl Hydroxysultaine, Decyl Glucoside, Sodium C14-16 Oleon Sulfonate, Xanthan Gum, Citric Acid, Potassium Hydroxide, Sodium Hyaluronate, Niacinamide, Sodium Sulfate, Avena Sativa (Oat) Kernel Extract, Sodium Lauroyl Lactylate, Glycolic Acid, Phenoxyethanol, Ceramide NP, Ceramide AP, Phytosphingosine, Cholesterol, Carbomer, Ceramide EOP

Questions or comments

1-888-768-2913

RECENT MAJOR CHANGES

Correcting the name of the Section Type from Route of Administration to Dosage and Administration